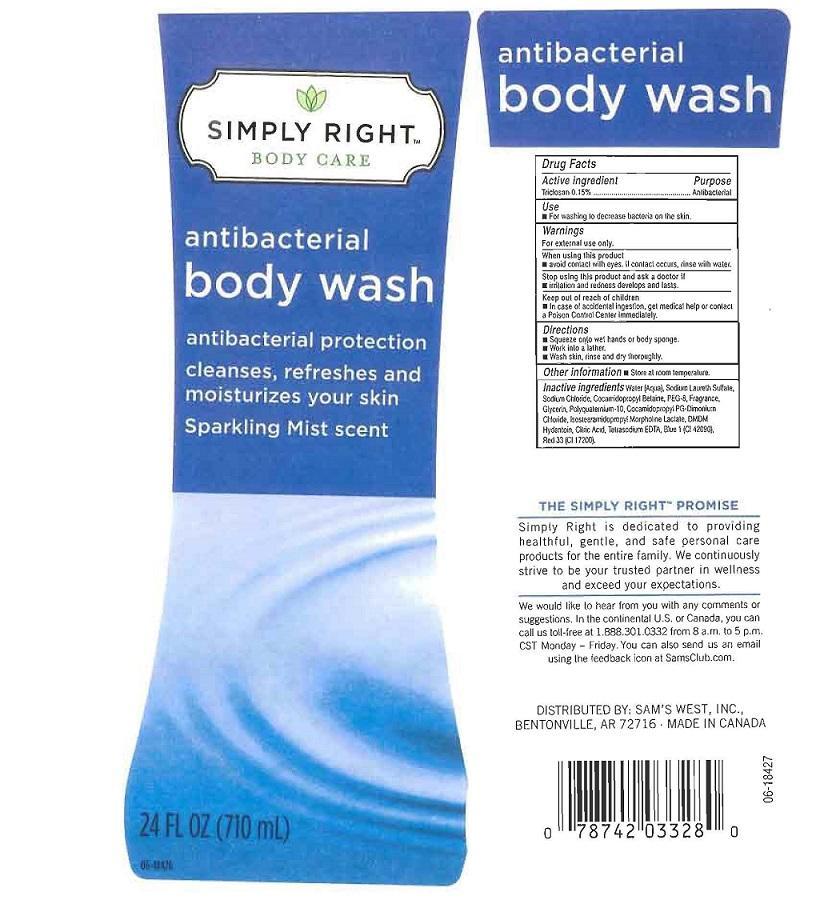 DRUG LABEL: SIMPLY RIGHT
NDC: 68196-808 | Form: LIQUID
Manufacturer: SAM'S WEST INC
Category: otc | Type: HUMAN OTC DRUG LABEL
Date: 20130812

ACTIVE INGREDIENTS: TRICLOSAN 1.5 mg/1 mL
INACTIVE INGREDIENTS: WATER; SODIUM LAURETH SULFATE; SODIUM CHLORIDE; COCAMIDOPROPYL BETAINE; POLYETHYLENE GLYCOL 400; GLYCERIN; POLYQUATERNIUM-10 (400 CPS AT 2%); COCAMIDOPROPYL PG-DIMONIUM CHLORIDE; ISOSTEARAMIDOPROPYL MORPHOLINE LACTATE; DMDM HYDANTOIN; CITRIC ACID MONOHYDRATE; EDETATE SODIUM; FD&C BLUE NO. 1; D&C RED NO. 33

DRUG FACTS

ACTIVE INGREDIENT

TRICLOSAN 0.15%

PURPOSE

ANTIBACTERIAL

USES

FOR WASHING TO DECREASE BACTERIA ON THE SKIN

WARNINGS

FOR EXTERNAL USE ONLY

WHEN USING THIS PRODUCT

AVOID CONTACT WITH EYES. IF CONTACT OCCURS RINSE WITH WATER

STOP USING THE PRODUCT AND ASK A DOCTOR IF

IRRITATION AND REDNESS DEVELOP AND LAST.

KEEP OUT OF REACH OF CHILDREN

IN CASE OF ACCIDENTAL INGESTION, GET MEDICAL HELP OR CONTACT A POISON CONTROL CENTER IMMEDIATELY

DIRECTIONS

SQUEEZE ONTO WET HANDS OR BODY SPONGE. WORK INTO A LATHER. WASH SKIN, RINSE AND DRY THOROUGHLY.

OTHER INFORMATION

STORE AT ROOM TEMPERATURE

INACTIVE INGREDIENTS:

WATER (AQUA), SODIUM LAURETH SULFATE, SODIUM CHLORIDE, COCAMIDOPROPYL BETAINE, PEG-8, FRAGRANCE, GLYCERIN, POLYQUATERNIUM-10, COCAMIDOPROPYL PG-DIMONIUM CHLORIDE,ISOSTEARAMIDOPROPYL MORPHOLINE LACTATE, DMDM HYDANTOIN, CITRIC ACIE, TETRASODIUM EDTA, BLUE 1(CI 42090), RED 33 (CI 17200).